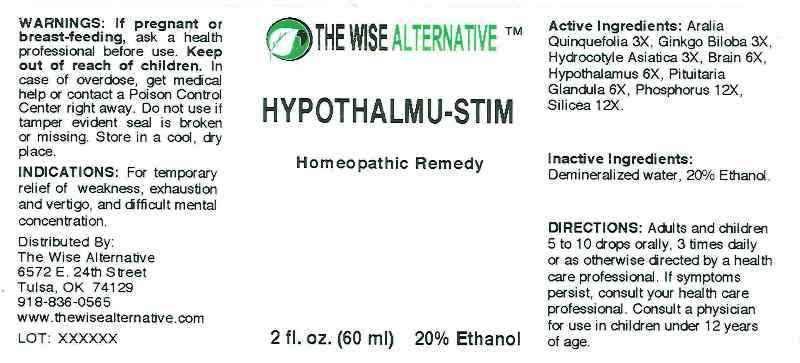 DRUG LABEL: Hypothalmu Stim
NDC: 51096-0002 | Form: LIQUID
Manufacturer: The Wise Alternative
Category: homeopathic | Type: HUMAN OTC DRUG LABEL
Date: 20121010

ACTIVE INGREDIENTS: AMERICAN GINSENG 3 [hp_X]/1 mL; GINKGO 3 [hp_X]/1 mL; CENTELLA ASIATICA 3 [hp_X]/1 mL; PORK BRAIN 6 [hp_X]/1 mL; SUS SCROFA HYPOTHALAMUS 6 [hp_X]/1 mL; SUS SCROFA PITUITARY GLAND 6 [hp_X]/1 mL; PHOSPHORUS 12 [hp_X]/1 mL; SILICON DIOXIDE 12 [hp_X]/1 mL
INACTIVE INGREDIENTS: WATER; ALCOHOL

Drug Facts

ACTIVE INGREDIENTS

Aralia Quinquefolia 3X, Ginkgo Biloba 3X, Hydrocotyle Asiatica 3X, Brain (Suis) 6X, Hypothalamus (Suis) 6X, Pituitary (Suis) 6X, Phosphorus 12X, Silicea 12X.

INDICATIONS

For temporary relief of weakness, exhaustion and vertigo and difficult mental concentration.

WARNINGS

If pregnant or breast feeding, ask a health professional before use. Keep out of reach of children. In case of overdose, get medical help or contact a Poison Control Center right away. Do not use if tamper evident seal is broken or missing. Store in a cool, dry place.

DIRECTIONS

Adults and children 5 to 10 drops orally. 3 times daily or as otherwise directed by a health care professional. If symptoms persist consult your health care professional. Consult a physician for use in children under 12 years of age.

INACTIVE INGREDIENTS

Demineralized water, 20% Ethanol.

KEEP OUT OF REACH OF CHILDREN

In case of overdose, get medical help or contact a Poison Control Center right away. Do not use if tamper evident seal is broken or missing. Store in a cool, dry place.

INDICATIONS AND USAGE

For temporary relief of weakness, exhaustion and vertigo and difficult mental concentration.

QUESTIONS

Distributed By:

The Wise Alternative

6572 E. 24th Street

Tulsa, OK 74129

918-836-0565

918-836-0565

PACKAGE LABEL

THE WISE ALTERNATIVE

Hypothalmu Stim

Homeopathic Remedy

2 fl. oz. (60 ml)